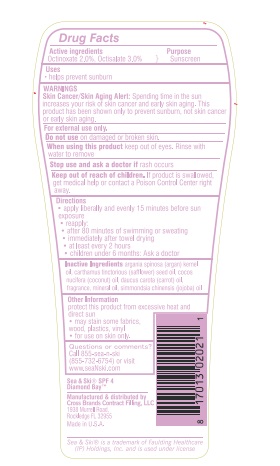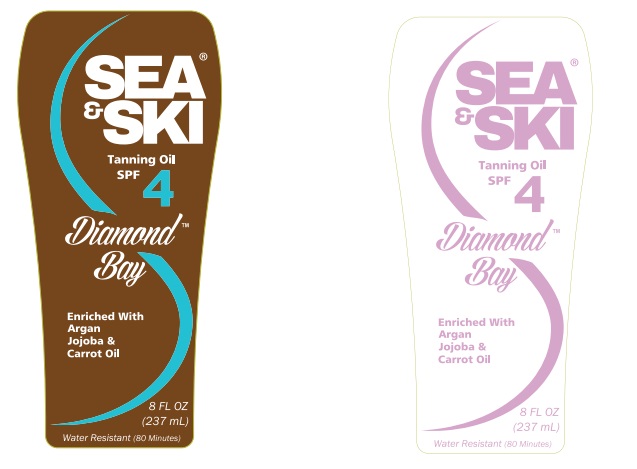 DRUG LABEL: Sea and Ski Tanning Oil SPF 4
NDC: 73440-2021 | Form: OIL
Manufacturer: Cross Brands Contract Filling
Category: otc | Type: HUMAN OTC DRUG LABEL
Date: 20210326

ACTIVE INGREDIENTS: OCTISALATE 6.9 g/230 g; OCTINOXATE 4.6 g/230 g
INACTIVE INGREDIENTS: MINERAL OIL 201.02 g/230 g

Sea & Ski Tanning Oil SPF 4